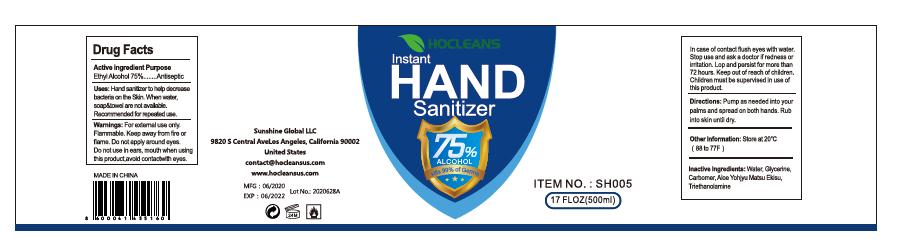 DRUG LABEL: Hocleans Instant Hand Sanitizer
NDC: 77907-002 | Form: GEL
Manufacturer: Hangzhou Yitong Biotech Co., Ltd.
Category: otc | Type: HUMAN OTC DRUG LABEL
Date: 20200610

ACTIVE INGREDIENTS: ALCOHOL 75 mL/100 mL
INACTIVE INGREDIENTS: WATER; GLYCERIN; PROPYLENE GLYCOL; TROLAMINE; .ALPHA.-TOCOPHEROL ACETATE, D-; ALOE VERA LEAF

Active ingredient

Ethyl Alcohol 75%

Purpose

Antiseptic

Use

Hand disinfectant help decrease bacteria & virus on the skin when water, soap & towel are not available. Recommended for repeated use.

Warnings

For external use only.

Flammable,

Keep away from fire or flame

Do not apply around eyes, do not use in ears and mouth.

When using this product

avoid contact with eyes. In case of contact, flush eyes with water.

Stop use and ask a doctor if

redness or irritation develop and persist for more than 72 hours

Keep out of reach of children.

Children must be supervised in use of this product.

Directions

Pump as needed into your palms and thoroughly spread on both hands. Rub into skin until dry.

Inactive ingredients

Water, Triethanolamine, glycerin, Propylene Glycol, Tocopheryl Acetate, Aloe Barbadensis Gel, Carbomer, Fragrance

Other information

Store between 20℃（68-77℉）

May discolor fabrics.